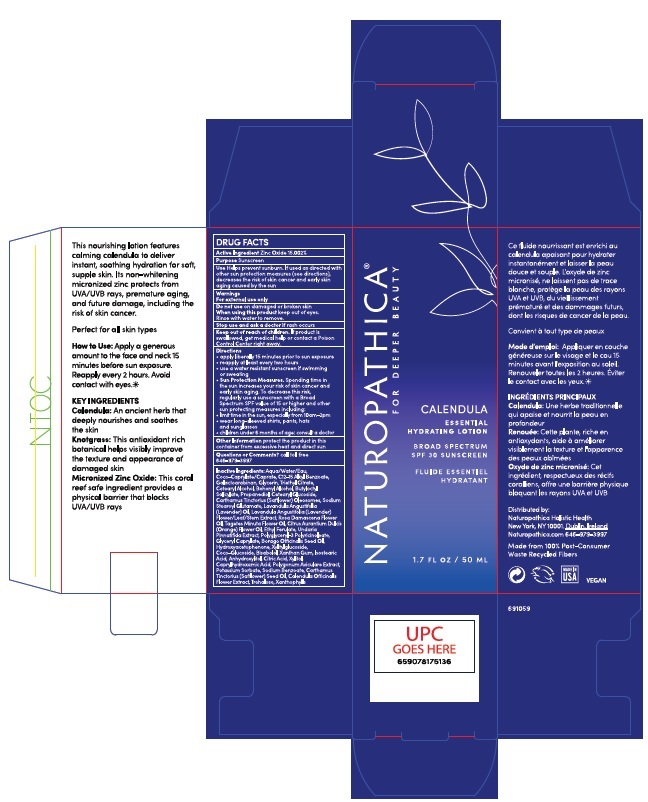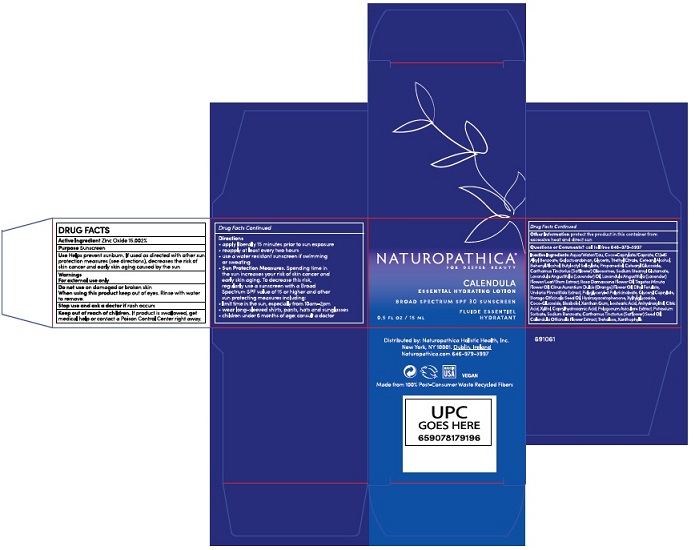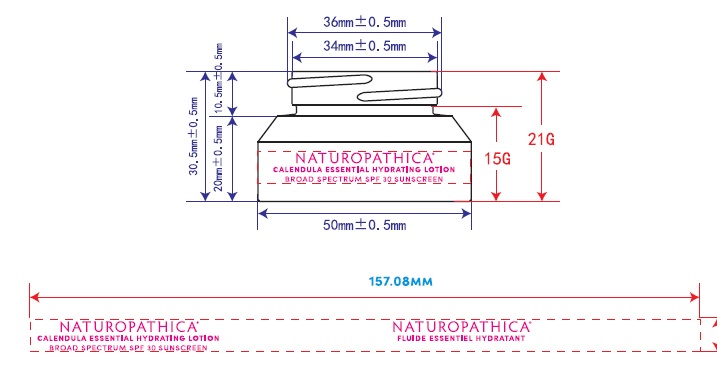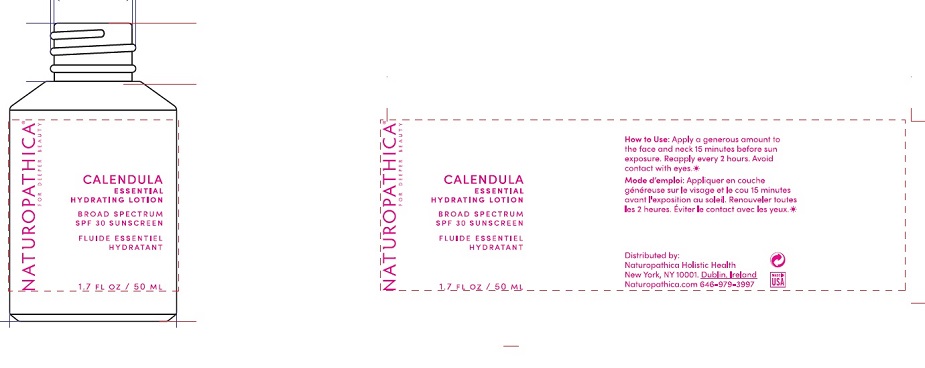 DRUG LABEL: Naturopathica
NDC: 54111-152 | Form: LOTION
Manufacturer: Bentley Laboratories, LLC
Category: otc | Type: HUMAN OTC DRUG LABEL
Date: 20210201

ACTIVE INGREDIENTS: ZINC OXIDE 15.002 g/100 mL
INACTIVE INGREDIENTS: WATER; COCO-CAPRYLATE/CAPRATE; ALKYL (C12-15) BENZOATE; GALACTOARABINAN; GLYCERIN; TRIETHYL CITRATE; CETOSTEARYL ALCOHOL; DOCOSANOL; BUTYLOCTYL SALICYLATE; PROPANEDIOL; CETEARYL GLUCOSIDE; CARTHAMUS TINCTORIUS (SAFFLOWER) OLEOSOMES; SODIUM STEAROYL GLUTAMATE; LAVENDER OIL; LAVANDULA ANGUSTIFOLIA SUBSP. ANGUSTIFOLIA FLOWERING TOP; ROSA DAMASCENA FLOWER OIL; TAGETES MINUTA FLOWER OIL; CITRUS SINENSIS FLOWER OIL; ETHYL FERULATE; UNDARIA PINNATIFIDA; POLYGLYCERYL-3 PENTARICINOLEATE; GLYCERYL CAPRYLATE; BORAGE SEED OIL; HYDROXYACETOPHENONE; XYLITYLGLUCOSIDE; COCO GLUCOSIDE; LEVOMENOL; XANTHAN GUM; ISOSTEARIC ACID; ANHYDROXYLITOL; CITRIC ACID MONOHYDRATE; XYLITOL; CAPRYLHYDROXAMIC ACID; POLYGONUM AVICULARE TOP; POTASSIUM SORBATE; SODIUM BENZOATE; SAFFLOWER OIL; CALENDULA OFFICINALIS FLOWER; TREHALOSE; LUTEIN

NATUROPATHICA CALENDULA ESSENTIAL HYDRATING LOTION

Drug Facts Active Ingredient

Zinc Oxide 15.002%

Purpose

Sunscreen

Uses

Helps prevent sunburn. If used as directed with

other sun protection measures (see Directions),

decreases the risk of skin cancer and early skin

aging caused by the sun

Warnings

For external use only
Do not use on damaged or broken skin
When using this product keep out of eyes.
Rinse with water to remove.
Stop use and ask a doctor if rash occurs

Keep out of reach of children. If product is

swallowed, get medical help or contact a Poison

Control Center right away.

Directions

• apply liberally 15 minutes before sun exposure
• reapply at least every two hours
• use a water resistant sunscreen if swimming or sweating
• Sun Protection Measures. Spending time in
the sun increases your risk of skin cancer and
early skin aging. To decrease this risk,
regularly use a sunscreen with a Broad
Spectrum SPF 15 or higher and other
sun protection measures including:
• limit time in the sun, especially from 10a.m. - 2p.m.
• wear long-sleeved shirts, pants, hats and sunglasses
• children under 6 months of age: consult a doctor

Other Information

Protect the product in this container from excessive heat and direct sun

Questions or Comments? call toll free 646-979-3997

Inactive Ingredients

Aqua/Water/Eau,
Coco-Caprylate/Caprate, C12-15 Alkyl Benzoate,
Galactoarabinan, Glycerin, Triethyl Citrate,
Cetearyl Alcohol, Behenyl Alcohol, Butyloctyl
Salicylate, Propanediol, Cetearyl Glucoside,
Carthamus Tinctorius (Safflower) Oleosomes, Sodium
Stearoyl Glutamate, Lavandula Angustifolia
(Lavender) Oil, Lavandula Angustifolia (Lavender)
Flower/Leaf/Stem Extract, Rosa Damascena Flower
Oil, Tagetes Minuta Flower Oil, Citrus Aurantium Dulcis
(Orange) Flower Oil, Ethyl Ferulate, Undaria
Pinnatifida Extract, Polyglyceryl-3 Polyricinoleate,
Glyceryl Caprylate, Borago Officinalis Seed Oil,
Hydroxyacetophenone, Xylitylglucoside,
Coco-Glucoside, Bisabolol, Xanthan Gum, Isostearic
Acid, Anhydroxylitol, Citric Acid, Xylitol,
Caprylhydroxamic Acid, Polygonum Aviculare Extract,
Potassium Sorbate, Sodium Benzoate, Carthamus
Tinctorius (Safflower) Seed Oil, Calendula Officinalis
Flower Extract, Trehalose, Xanthophylls

Product Label

NATUROPATHICA®

FOR DEEPER BEAUTY

CALENDULA

ESSENTIAL

HYDRATING LOTION

BROAD SPECTRUM

SPF 30 SUNSCREEN

FLUIDE ESSENTIAL

HYDRATANT

1.7 Fl. OZ /50 ML

Distributed by:

Naturopathica Holistic Health

New York, NY 10001. Dublin, Ireland

Naturopathica.com 646-979-3997

1.7 Fl OZ

0.5 Fl OZ

res